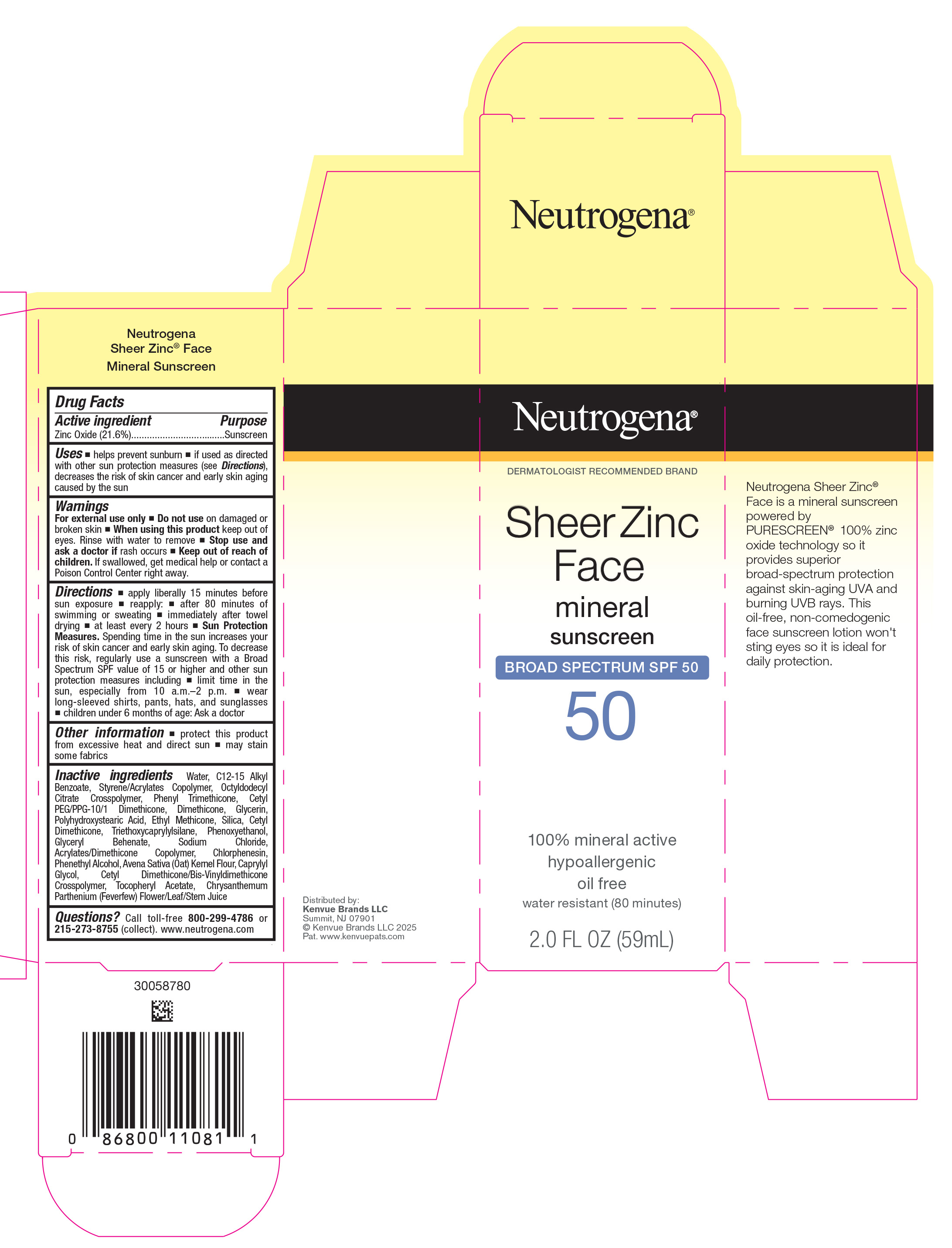 DRUG LABEL: Neutrogena Sheer Zinc Face Mineral Sunscreen Broad Spectrum SPF 50
NDC: 69968-0623 | Form: LOTION
Manufacturer: Kenvue Brands LLC
Category: otc | Type: HUMAN OTC DRUG LABEL
Date: 20250605

ACTIVE INGREDIENTS: ZINC OXIDE 216 mg/1 mL
INACTIVE INGREDIENTS: CETYL PEG/PPG-10/1 DIMETHICONE (HLB 5); DIMETHICONE; GLYCERIN; POLYHYDROXYSTEARIC ACID (2300 MW); ETHYL METHICONE (8 MPA.S); SILICON DIOXIDE; CETYL DIMETHICONE 25; TRIETHOXYCAPRYLYLSILANE; PHENOXYETHANOL; GLYCERYL DIBEHENATE; SODIUM CHLORIDE; CHLORPHENESIN; PHENYLETHYL ALCOHOL; OATMEAL; CAPRYLYL GLYCOL; CETYL DIMETHICONE/BIS-VINYLDIMETHICONE CROSSPOLYMER; .ALPHA.-TOCOPHEROL ACETATE; FEVERFEW; WATER; ALKYL (C12-15) BENZOATE; BUTYL METHACRYLATE/METHYL METHACRYLATE/METHACRYLIC ACID/STYRENE CROSSPOLYMER; OCTYLDODECYL CITRATE CROSSPOLYMER; PHENYL TRIMETHICONE

Neutrogena® Sheer Zinc Face mineral sunscreen BROAD SPECTRUM SPF 50

Drug Facts

Active ingredient

Zinc Oxide (21.6%)

Purpose

Sunscreen

Uses

- helps prevent sunburn
- if used as directed with other sun protection measures (see Directions), decreases the risk of skin cancer and early skin aging caused by the sun

Warnings

For external use only

- Do not use on damaged or broken skin

- When using this product keep out of eyes. Rinse with water to remove

- Stop use and ask a doctor if rash occurs

- Keep out of reach of children. If swallowed, get medical help or contact a Poison Control Center right away.

Directions

- apply liberally 15 minutes before sun exposure
- reapply:
  - after 80 minutes of swimming or sweating
  - immediately after towel drying
  - at least every 2 hours
- Sun Protection Measures. Spending time in the sun increases your risk of skin cancer and early skin aging. To decrease this risk, regularly use a sunscreen with a Broad Spectrum SPF value of 15 or higher and other sun protection measures including:
  - limit time in the sun, especially from 10 a.m. – 2 p.m.
  - wear long-sleeved shirts, pants, hats, and sunglasses
- children under 6 months of age: Ask a doctor

Other information

- protect this product from excessive heat and direct sun
- may stain some fabrics

Inactive ingredients

Water, C12-15 Alkyl Benzoate, Styrene/Acrylates Copolymer, Octyldodecyl Citrate Crosspolymer, Phenyl Trimethicone, Cetyl PEG/PPG-10/1 Dimethicone, Dimethicone, Glycerin, Polyhydroxystearic Acid, Ethyl Methicone, Silica, Cetyl Dimethicone, Triethoxycaprylylsilane, Phenoxyethanol, Glyceryl Behenate, Sodium Chloride, Acrylates/Dimethicone Copolymer, Chlorphenesin, Phenethyl Alcohol, Avena Sativa (Oat) Kernel Flour, Caprylyl Glycol, Cetyl Dimethicone/Bis-Vinyldimethicone Crosspolymer, Tocopheryl Acetate, Chrysanthemum Parthenium (Feverfew) Flower/Leaf/Stem Juice

Questions?

Call toll-free 800-299-4786 or 215-273-8755 (collect). www.neutrogena.com

Distributed by:

Kenvue Brands LLC

Summit, NJ 07901

PRINCIPAL DISPLAY PANEL - 59 mL Tube Carton

Neutrogena®
DERMATOLOGIST RECOMMENDED BRAND

Sheer Zinc
Face
mineral
sunscreen
BROAD SPECTRUM SPF 50
50

100% mineral active
hypoallergenic
oil free
water resistant (80 minutes)

2.0 FL OZ (59mL)